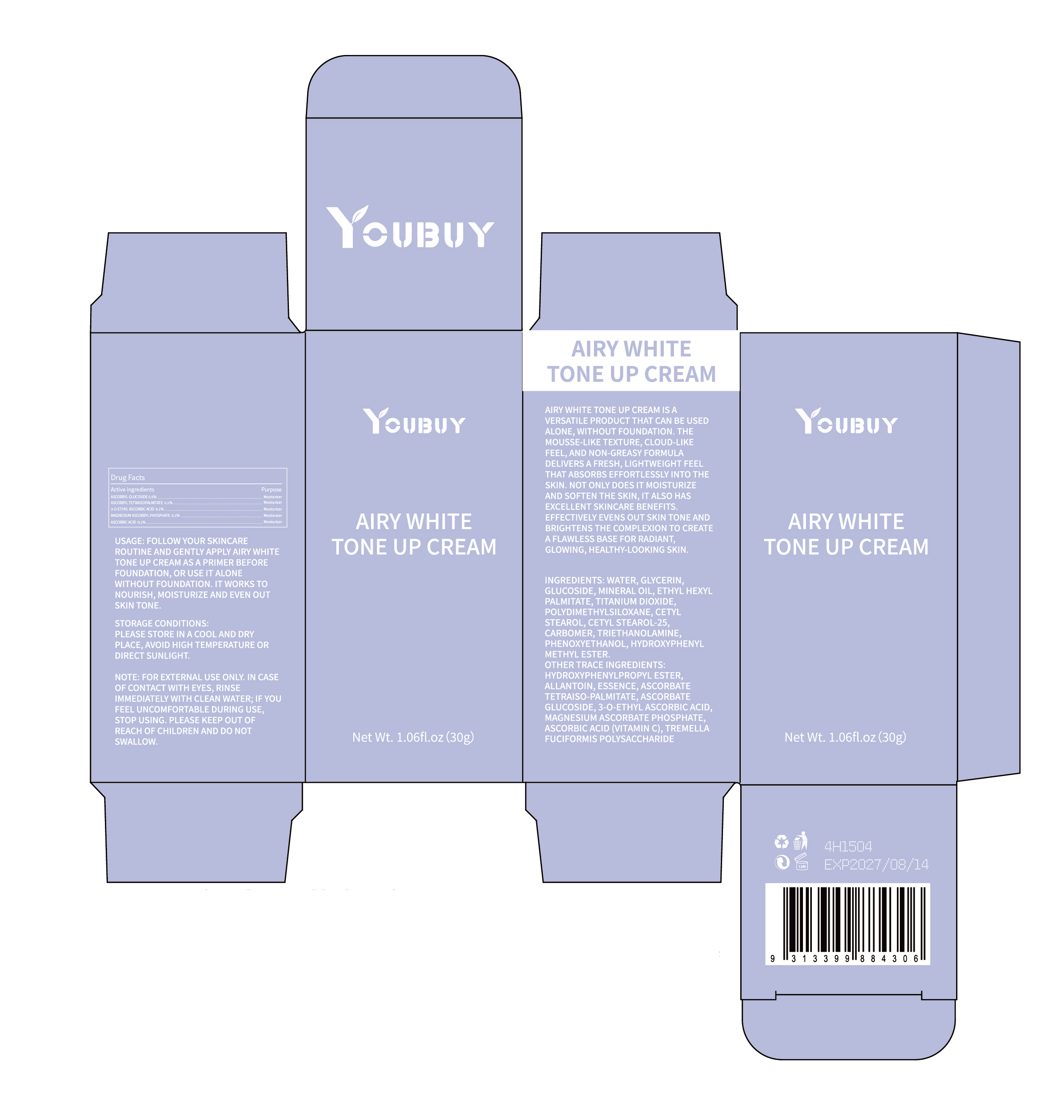 DRUG LABEL: YOUBUY Airy White Tone Up Cream
NDC: 84712-027 | Form: CREAM
Manufacturer: Guangdong Youbaijia Cosmetic Industry Co., Ltd
Category: otc | Type: HUMAN OTC DRUG LABEL
Date: 20241028

ACTIVE INGREDIENTS: MAGNESIUM ASCORBYL PHOSPHATE 0.03 g/30 g; ASCORBYL TETRAISOPALMITATE 0.03 g/30 g; ASCORBYL GLUCOSIDE 0.03 g/30 g; ASCORBIC ACID 0.03 g/30 g; 3-O-ETHYL ASCORBIC ACID 0.03 g/30 g
INACTIVE INGREDIENTS: GLYCERIN 1.5 g/30 g

ACTIVE INGREDIENT

ASCORBYL GLUCOSIDE 0.1%
ASCORBYL TETRAISOPALMITATE 0.1%
3-O-ETHYL ASCORBIC ACID 0.1%
MAGNESIUM ASCORBYL PHOSPHATE 0.1%
ASCORBIC ACID 0.1%

INACTIVE INGREDIENT

WATER
GLYCERIN
GLYCERYL GLUCOSIDE
MINERAL OIL
ETHYLHEXYL PALMITATE
TITANIUM DIOXIDE
DIMETHICONE
CETEARYL ALCOHOL
CETEARETH-25
CARBOMER
TRIETHANOLAMINE
PHENOXYETHANOL
METHYLPARABEN
PROPYLPARABEN
ALLANTOIN
PARFUM
TREMELLA FUCIFORMIS POLYSACCHARIDE

Keep away from children. Do not swallow.

PURPOSE

MOISTURIZE AND SOFTEN THE SKIN

QUESTIONS

Contact name: Jessie Peng
Company phone number: +1 818 579 7288
Company e-mail: jessie@registeragentllc.com

STOP USE

lf skin becomes red or irritated, discontinue use immediately and wash with water.

Do not use on damaged skin.

WHEN USING

keep out of eyes. Rinse with water to remove.

STORAGE AND HANDLING

Storage conditions:Keep away from light and in a dry place.

DOSAGE AND ADMINISTRATION

USAGE: FOLLOW YOUR SKINCARE ROUTINE AND GENTLY APPLY AIRY WHITE TONE UP CREAM AS A PRIMER BEFORE FOUNDATION, OR USE IT ALONE WITHOUT FOUNDATION.IT WORKS TO NOURISH,MOISTURIZE AND EVEN OUT SKIN TONE

WARNINGS

For external use only.

INDICATIONS AND USAGE

AIRY WHITE TONE UP CREAM IS A VERSATILE PRODUCT THAT CAN BE USED ALONE,WITHOUT FOUNDATION.THE MOUSSE-LIKE TEXTURE,CLOUD-LIKE FEEL, AND NON-GREASY FORMULA DELIVERS A FRESH,LIGHTWEIGHT FEEL THAT ABSORBS EFFORTLESSLY INTO THE SKIN. NOT ONLY DOES IT MOISTURIZE AND SOFTEN THE SKIN,IT ALSO HAS EXCELLENT SKINCARE BENEFITSEFFECTIVELY EVENS OUT SKIN TONE AND BRIGHTENS THE COMPLEXION TO CREATE A FLAWLESS BASE FOR RADIANT,GLOWING, HEALTHY-LOOKING SKIN.